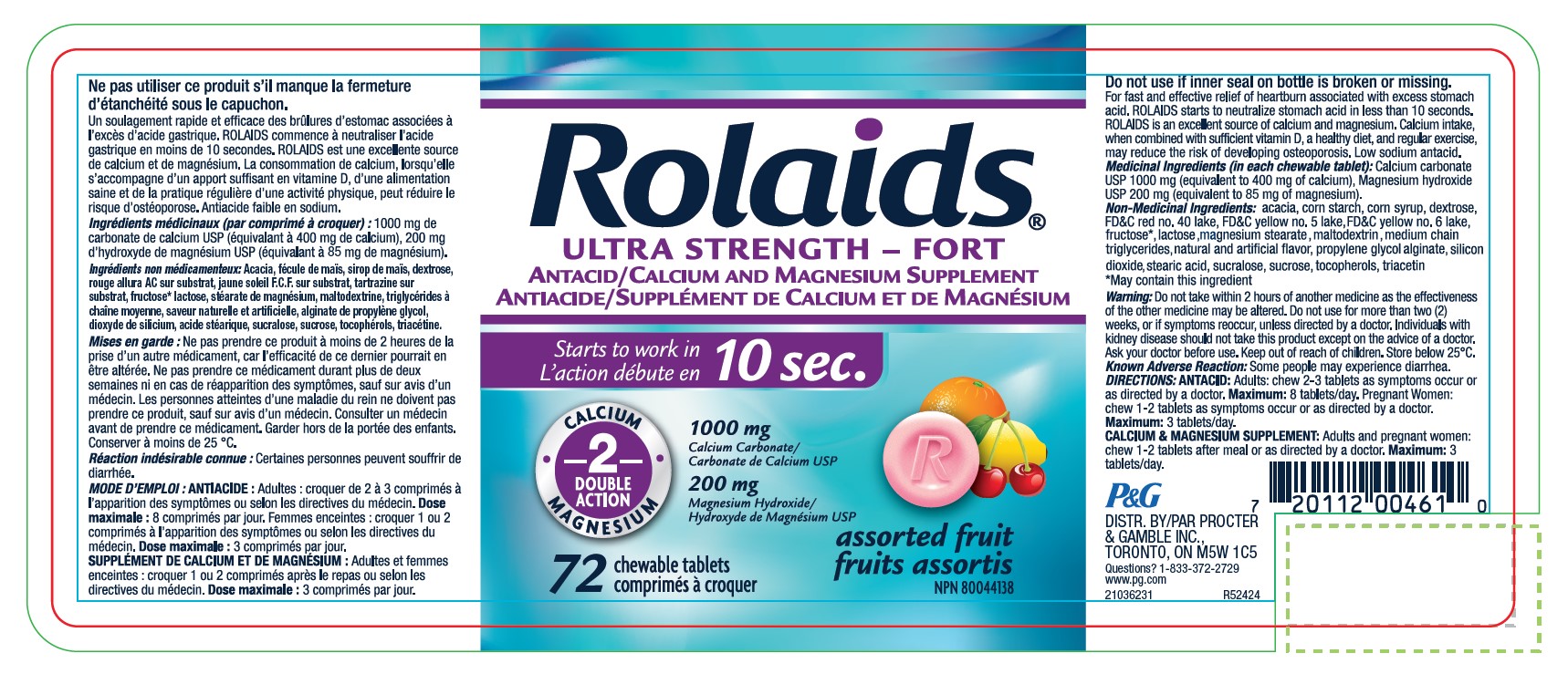 DRUG LABEL: Calcium Carbonate, Magnesium Hydroxide
NDC: 10267-0039 | Form: TABLET, CHEWABLE
Manufacturer: Contract Pharmacal Corp.
Category: otc | Type: HUMAN OTC DRUG LABEL
Date: 20250325

ACTIVE INGREDIENTS: CALCIUM CARBONATE 1000 mg/1 1; MAGNESIUM HYDROXIDE 200 mg/1 1
INACTIVE INGREDIENTS: STARCH, CORN; MEDIUM-CHAIN TRIGLYCERIDES; DEXTROSE; CORN SYRUP; FRUCTOSE; LACTOSE, UNSPECIFIED FORM; MAGNESIUM STEARATE; SILICON DIOXIDE; ACACIA; PROPYLENE GLYCOL ALGINATE; MALTODEXTRIN; FD&C YELLOW NO. 6 ALUMINUM LAKE; FD&C RED NO. 40; TOCOPHEROL; TRIACETIN; STEARIC ACID; FD&C YELLOW NO. 5 ALUMINUM LAKE; SUCRALOSE; SUCROSE

5931- Export